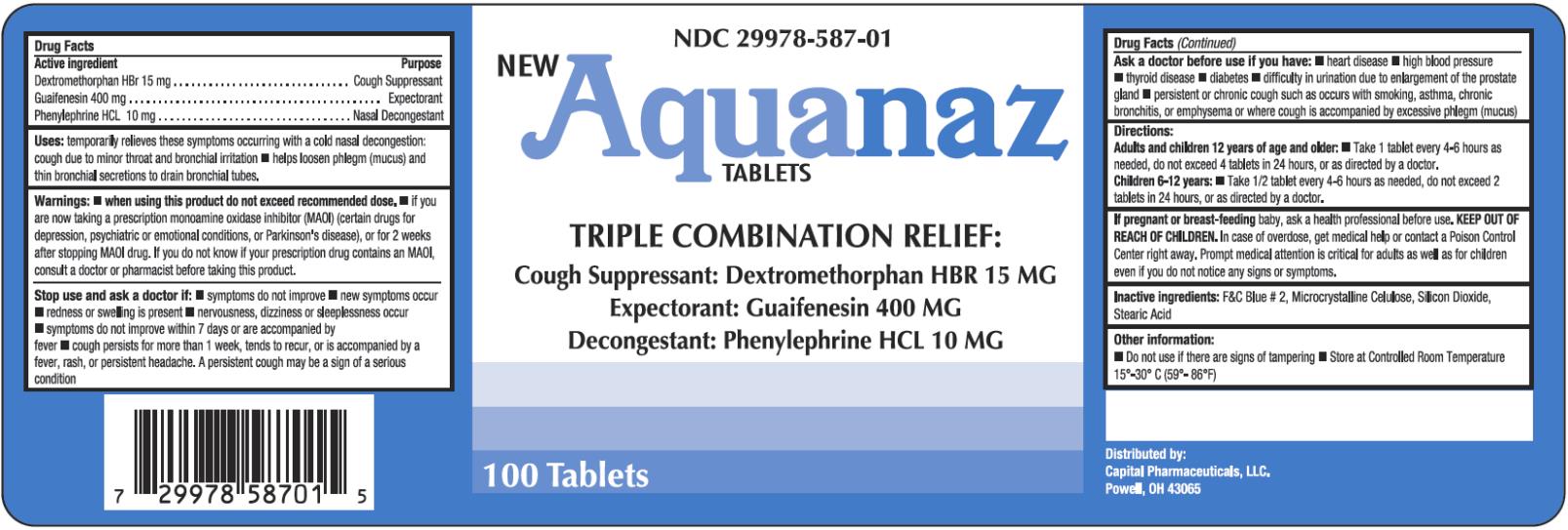 DRUG LABEL: Aquanaz
NDC: 29978-587 | Form: TABLET
Manufacturer: Capital Pharmaceutical, LLC
Category: otc | Type: HUMAN OTC DRUG LABEL
Date: 20251126

ACTIVE INGREDIENTS: DEXTROMETHORPHAN HYDROBROMIDE 15 mg/1 1; GUAIFENESIN 400 mg/1 1; PHENYLEPHRINE HYDROCHLORIDE 10 mg/1 1
INACTIVE INGREDIENTS: FD&C BLUE NO. 2; CELLULOSE, MICROCRYSTALLINE; SILICON DIOXIDE; STEARIC ACID

Aquanaz Tablets

Aquanaz Drug Facts.

Active Ingredient.

Dextromethorphan HBr 15mg.

Purpose.

Cough Suppressant.

Active Ingredient.

Guaifenesin 400mg.

Purpose.

Expectorant.

Active Ingredient.

Phenylephrine HCL 10mg.

Purpose.

Nasal Decongestant.

Uses:

Temporally relieves these symptoms accruing with a cold nasal decongestion cough due to minor throat and bronchial irritation—helps loosen phlegm (mucus) and thins bronchial secretions to drain bronchial tubes.

Warnings: When using this product do not exceed recommended dose.

If you are now taking a prescription monoamine oxidase inhibitor (MAOI) (Certain drugs for depression, psychiatric or emotional conditions, or Parkinson’s disease), or for 2 weeks after stopping MAOI drugs. If you do not know if your prescription drug contains an MAOI. Consult a doctor or pharmacist before taking this product.

Stop use and ask a doctor if:

Symptoms do not improve--new symptoms occur--redness or swelling is present--nervousness, dizziness or sleeplessness occurs--symptoms do not improve within 7 days or are accompanied by fever--cough persists for more than 1 week, tends to recur, or is a accompanied by fever, rash or persistent headache. A persistent cough may be the sign of a serious condition.

Ask a doctor before use if you have:

Heart disease--high blood pressure--thyroid disease—diabetes--difficulty in urination due to enlargement of the prostate gland—persistent or chronic cough such as occurs with smoking, asthma, chronic bronchitis or emphysema or where cough is accompanied by excessive phlegm (mucus)

Directions:

Adults and children 12 years and older: Take 1tablet every 4-6 hours as needed, do not exceed 4 tablets in 24hours, or as directed by a doctor.

Children 6-12 years: Take ½ tablet every 4-6 hours as needed, do not exceed 2 tablets in 24 hours, or as directed by a doctor.

If pregnant or breast-feeding baby,

ask a health care professional before use.

KEEP OUT OF REACH OF CHILDREN.

In case of overdose, get medical help or contact a Poison Control Center right away. Prompt medical attention is critical for adults as well as children even if you do not notice any signs or symptoms.

Inactive Ingredients:

F&C Blue #2 Microcrystalline Celulose, Silicone Dioxide, Stearic Acid.

Other Information:

Do not use if there are signs of tampering—Store at controlled room temperature 15deg-30degC (59-86degF)

PRINCIPAL DISPLAY PANEL

NDC 29978-587-01
NEW
Aquanaz
TABLETS
TRIPLE COMBINATION RELIEF:
Cough Suppressant: Dextromethorphan HBR 15 MG
Expectorant: Guaifenesin 400 MG
Decongestant: Phenylephrine HCL 10 MG
100 Tablets